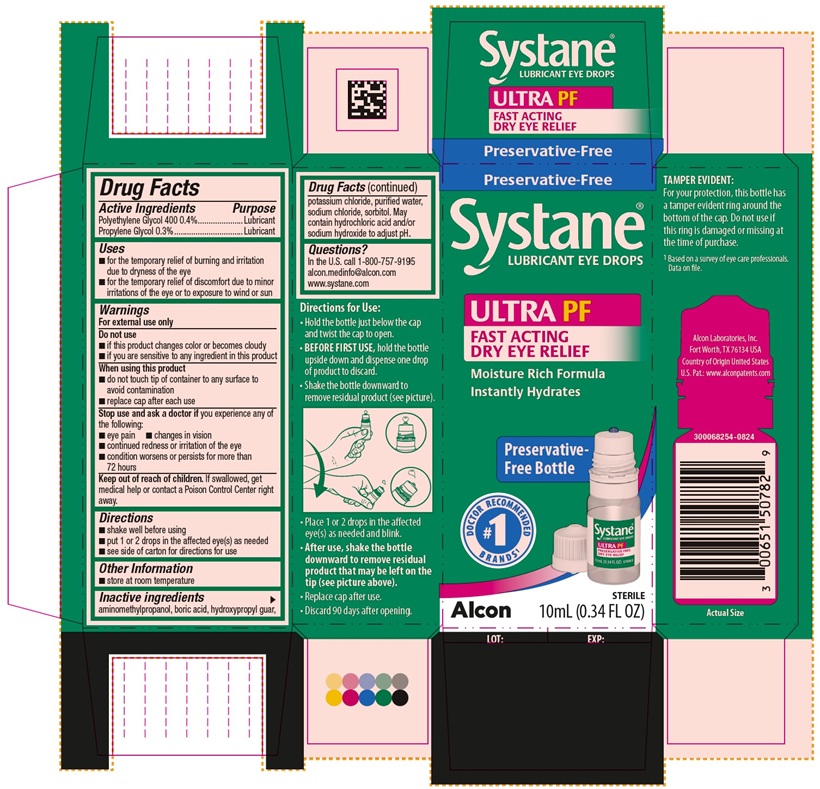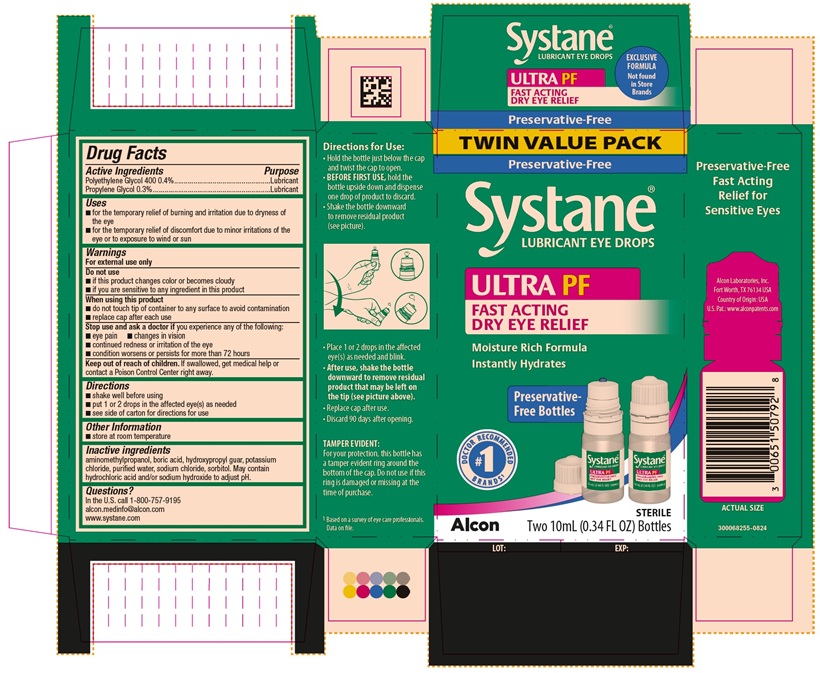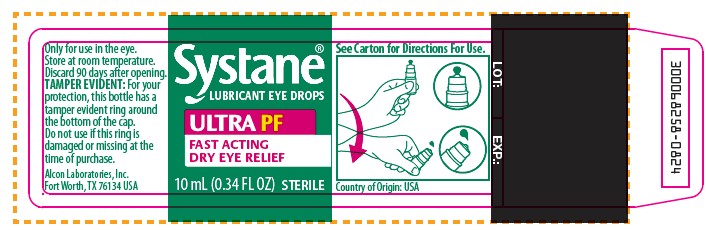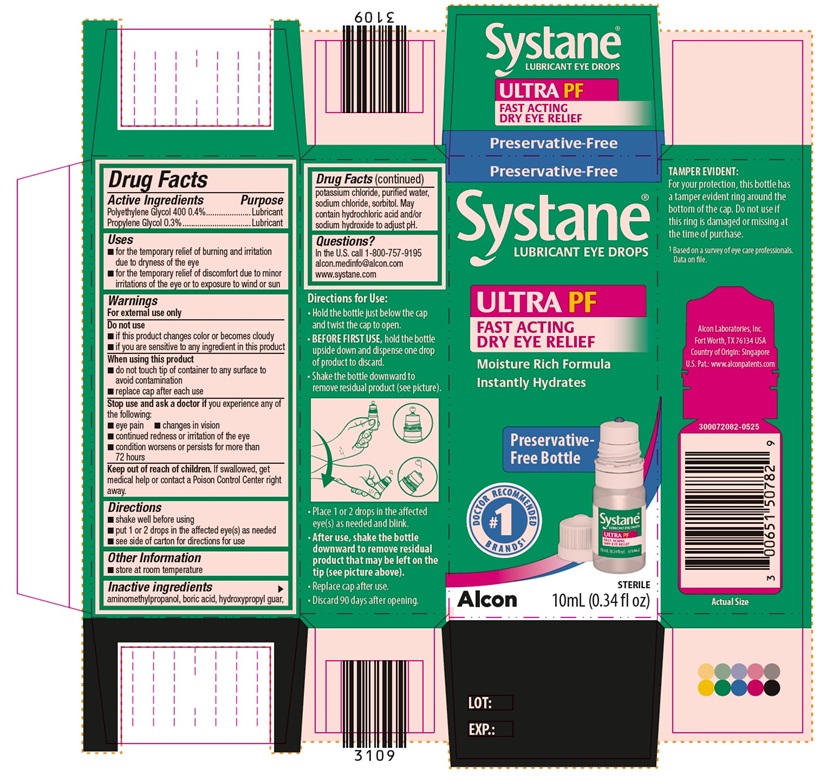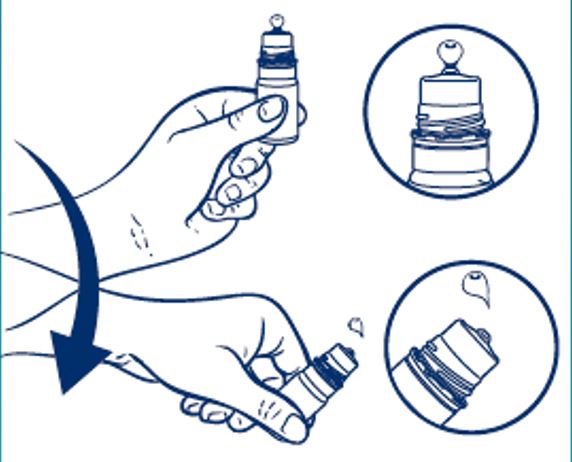 DRUG LABEL: Systane Ultra Preservative Free
NDC: 0065-1507 | Form: SOLUTION/ DROPS
Manufacturer: Alcon Laboratories, Inc.
Category: otc | Type: HUMAN OTC DRUG LABEL
Date: 20250730

ACTIVE INGREDIENTS: Polyethylene Glycol 400 4 mg/1 mL; Propylene Glycol 3 mg/1 mL
INACTIVE INGREDIENTS: Aminomethylpropanol; Boric Acid; Guaraprolose (3500 Mpa.S At 1%); Potassium Chloride; Water; Sodium Chloride; Sorbitol; Hydrochloric Acid; Sodium Hydroxide

Drug Facts

Active Ingredients | Purpose
Polyethylene Glycol 400 0.4% | Lubricant
Propylene Glycol 0.3% | Lubricant

Uses

- for the temporary relief of burning and irritation due to dryness of the eye
- for the temporary relief of discomfort due to minor irritations of the eye or to exposure to wind or sun

Warnings

For external use only

Do not use

- if this product changes color or becomes cloudy
- if you are sensitive to any ingredient in this product

When using the product

- do not touch tip of container to any surface to avoid contamination
- replace cap after each use

Stop use and ask a doctor if you experience any of the following:

- eye pain
- changes in vision
- continued redness or irritation of the eye
- condition worsens or persists for more than 72 hours

Keep out of reach of children.

If swallowed, get medical help or contact a Poison Control Center right away.

Directions

- shake well before using
- put 1 or 2 drops in the affected eye(s) as needed
- see side of carton for directions for use

Other Information

- Store at room temperature

Inactive ingredients

Aminomethylpropanol, boric acid, hydroxypropyl guar, potassium chloride, purified water, sodium chloride, sorbitol. May contain hydrochloric acid and/or sodium hydroxide to adjust pH.

Questions?

In the U.S. call 1-800-757-9195
alcon.medinfo@alcon.com
www.systane.com

Directions for Use:

- Hold the bottle just below the cap and twist the cap to open.
- BEFORE FIRST USE, hold the bottle upside down and dispense one drop of product to discard.
- Shake the bottle downward to remove residual product (see picture).

- Place 1 or 2 drops in the affected eye(s) as needed and blink.
- After use, shake the bottle downward to remove residual product that may be left on the tip (see picture above).
- Replace cap after use.
- Discard 90 days after opening.

PRINCIPAL DISPLAY PANEL

Preservative-Free
Systane®
LUBRICANT EYE DROPS
ULTRA PF
FAST ACTING
DRY EYE RELIEF
Moisture Rich Formula
Instantly Hydrates
Preservative-Free Bottle
DOCTOR RECOMMENDED #1 BRANDS^1
Alcon
STERILE
10 mL (0.34 FL OZ)
LOT: EXP.:
SIDE PANEL:
TAMPER EVIDENT:
For your protection, this bottle has a tamper evident ring around the bottom of the cap. Do not use if this ring is damaged or missing at the time of purchase.
^1Based on a survey of eye care professionals. Data on file.
Alcon Laboratories, Inc.
Fort Worth, TX 76134 USA
Country of Origin United States
U.S. Pat.: www.alconpatents.com
300068254-0824
Actual Size

TWIN VALUE PACK
Preservative-Free
Systane®
LUBRICANT EYE DROPS
ULTRA PF
FAST ACTING
DRY EYE RELIEF
Moisture Rich Formula
Instantly Hydrates
Preservative-Free Bottles
DOCTOR RECOMMENDED #1 BRANDS^1
Alcon
STERILE
Two 10 mL (0.34 FL OZ) Bottles
LOT: EXP.:
SIDE PANEL:
TAMPER EVIDENT:
For your protection, this bottle has a tamper evident ring around the bottom of the cap. Do not use if this ring is damaged or missing at the time of purchase.
^1Based on a survey of eye care professionals. Data on file.
Preservative-Free
Fast Acting
Relief for
Sensitive Eyes
Alcon Laboratories, Inc.
Fort Worth, TX 76134 USA
Country of Origin USA
U.S. Pat.: www.alconpatents.com
ACTUAL SIZE
300068255-0824

Preservative-Free
Systane®
LUBRICANT EYE DROPS
ULTRA PF
FAST ACTING
DRY EYE RELIEF
Moisture Rich Formula
Instantly Hydrates
Preservative-Free Bottle
DOCTOR RECOMMENDED #1 BRANDS^1
Alcon
STERILE
10 mL (0.34 fl oz)
LOT: EXP.:
SIDE PANEL:
TAMPER EVIDENT:
For your protection, this bottle has a tamper evident ring around the bottom of the cap. Do not use if this ring is damaged or missing at the time of purchase.
^1Based on a survey of eye care professionals. Data on file.
Alcon Laboratories, Inc.
Fort Worth, TX 76134 USA
Country of Origin: Singapore
U.S. Pat.: www.alconpatents.com
300072082-0525
Actual Size

Systane®
LUBRICANT EYE DROPS
ULTRA PF
FAST ACTING
DRY EYE RELIEF
10 mL (0.34 FL OZ) STERILE
Only for use in the eye.
Store at room temperature.
Discard 90 days after opening.
TAMPER EVIDENT: For your protection, this bottle has a tamper evident ring around the bottom of the cap. Do not use if this ring is damaged or missing at the time of purchase.
Alcon Laboratories, Inc.
Fort Worth, TX 76134 USA
See Carton for Directions For Use.
Country of Origin: USA
LOT: EXP:
300068258-0824